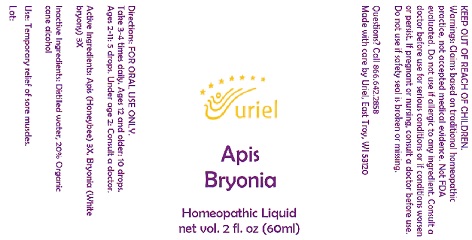 DRUG LABEL: Apis Bryonia
NDC: 48951-1355 | Form: LIQUID
Manufacturer: Uriel Pharmacy Inc.
Category: homeopathic | Type: HUMAN OTC DRUG LABEL
Date: 20220222

ACTIVE INGREDIENTS: APIS MELLIFERA 3 [hp_X]/1 mL; BRYONIA ALBA ROOT 3 [hp_X]/1 mL
INACTIVE INGREDIENTS: WATER; ALCOHOL

Apis Bryonia

DOSAGE AND ADMINISTRATION

Take 3-4 times daily. Ages 12 and older: 10 drops. Ages 2-11: 5 drops. Under age 2: Consult a doctor.

PURPOSE

Use: Temporary relief of sore muscles.

KEEP OUT OF REACH OF CHILDREN.